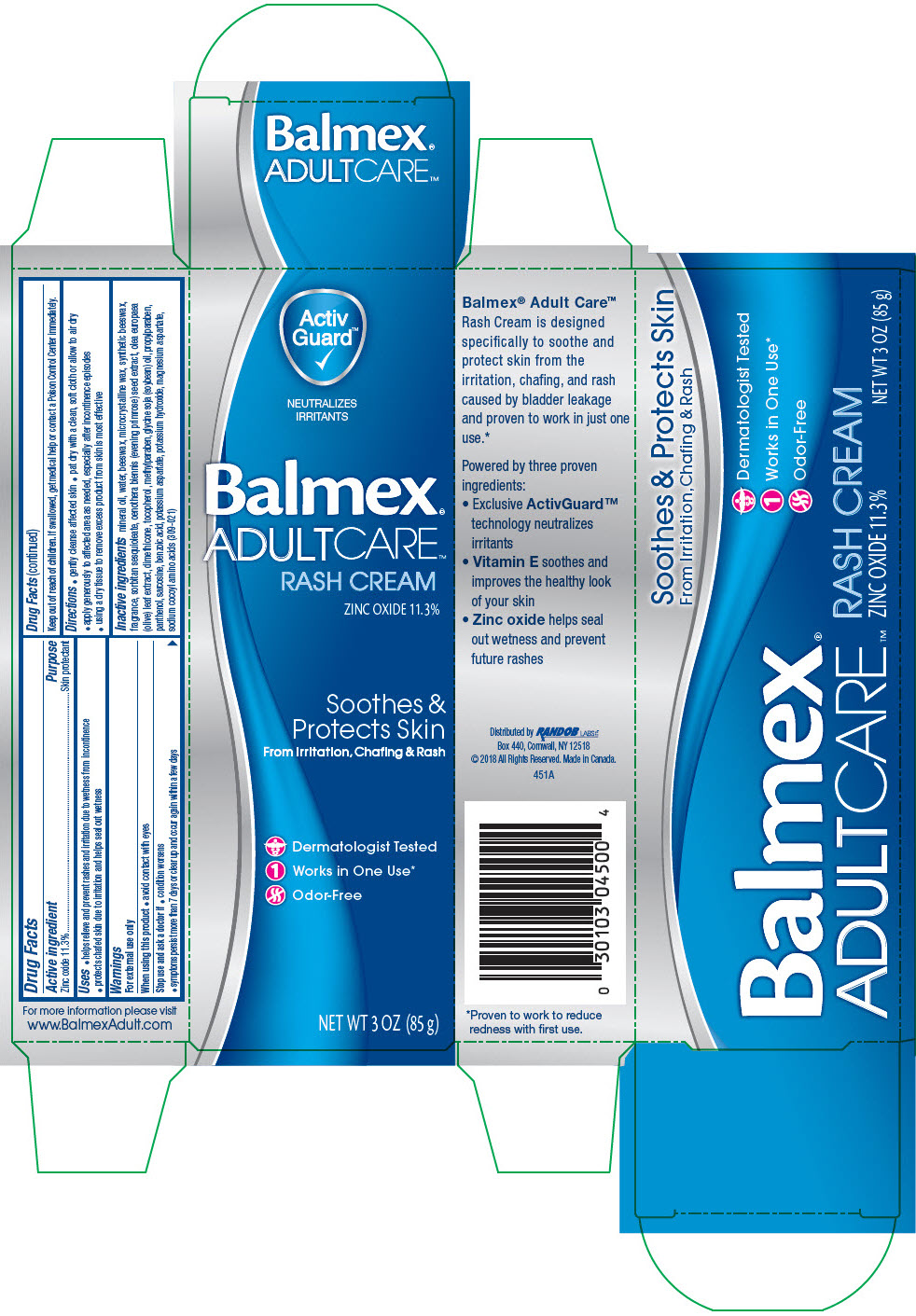 DRUG LABEL: BALMEX ADULT CARE RASH
NDC: 52412-500 | Form: CREAM
Manufacturer: Randob Labs,Ltd.
Category: otc | Type: HUMAN OTC DRUG LABEL
Date: 20181113

ACTIVE INGREDIENTS: Zinc Oxide 0.113 g/1 g
INACTIVE INGREDIENTS: Mineral Oil; Water; Yellow Wax; Microcrystalline Wax; Sorbitan Sesquioleate; Oenothera Biennis; Olea Europaea Leaf; Dimethicone 100; Tocopherol; Methylparaben; Soybean Oil; Propylparaben; Dexpanthenol; Sarcosine; Benzoic Acid; Potassium Aspartate; Potassium Hydroxide; Magnesium Aspartate Anhydrous; Sodium Cocoyl Glycinate; Propylene Glycol; White Wax

BALMEX® ADULT CARE™ RASH

Drug Facts

ACTIVE INGREDIENT

Active Ingredients | Purpose
Zinc Oxide 11.3% | Skin protectant

Uses

- helps relieve and prevent rashes and irritation due to wetness from incontinence
- protects chafed skin due to irritation and helps seal out wetness

Warnings

For external use only

When using this product

- avoid contact with eyes

Stop use and ask a doctor if

- condition worsens
- symptoms persist more than 7 days or clear up and occur again within a few days

Keep out of reach of children.

If swallowed, get medical help or contact a Poison Control Center immediately.

Directions

- gently cleanse affected skin
- pat dry with a clean, soft cloth or allow to air dry
- apply generously to affected area as needed, especially after incontinence episodes
- using a dry tissue to remove excess product from skin is most effective

INACTIVE INGREDIENT

Inactive ingredients mineral oil, water, beeswax, microcrystalline wax, synthetic beeswax, fragrance, sorbitan sesquioleate, oenothera biennis (evening primrose) seed extract, olea europaea (olive) leaf extract, dimethicone, tocopherol, methylparaben, glycine soja (soybean) oil, propylparaben, panthenol, sarcosine, benzoic acid, potassium aspartate, potassium hydroxide, magnesium aspartate, sodium cocoyl amino acids (309-021)

QUESTIONS

For more information please visit
www.BalmexAdult.com

Distributed by RANDOB LABS LTD.
Box 440, Cornwall, NY 12518

PRINCIPAL DISPLAY PANEL - 85 g Tube Carton

Activ
Guard™

NEUTRALIZES
IRRITANTS

Balmex®
ADULTCARE™

RASH CREAM
ZINC OXIDE 11.3%

Soothes &
Protects Skin
From Irritation, Chafing & Rash

Dermatologist Tested
Works in One Use*
Odor-Free

NET WT 3 OZ (85 g)